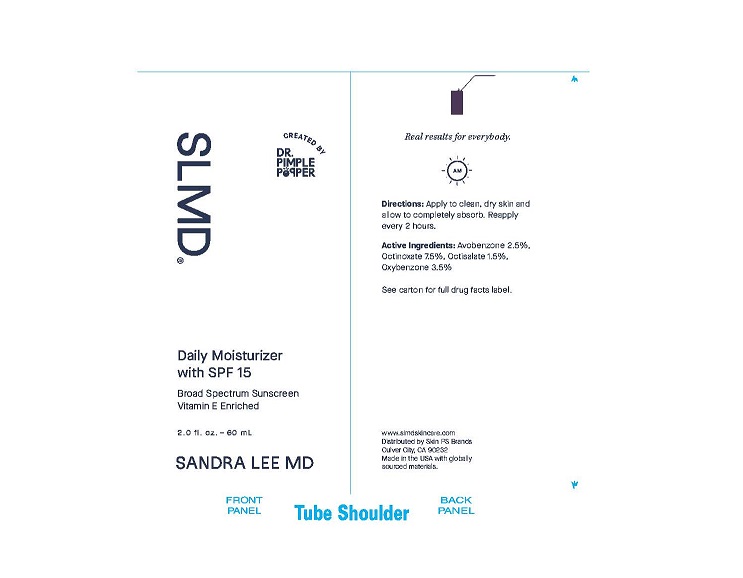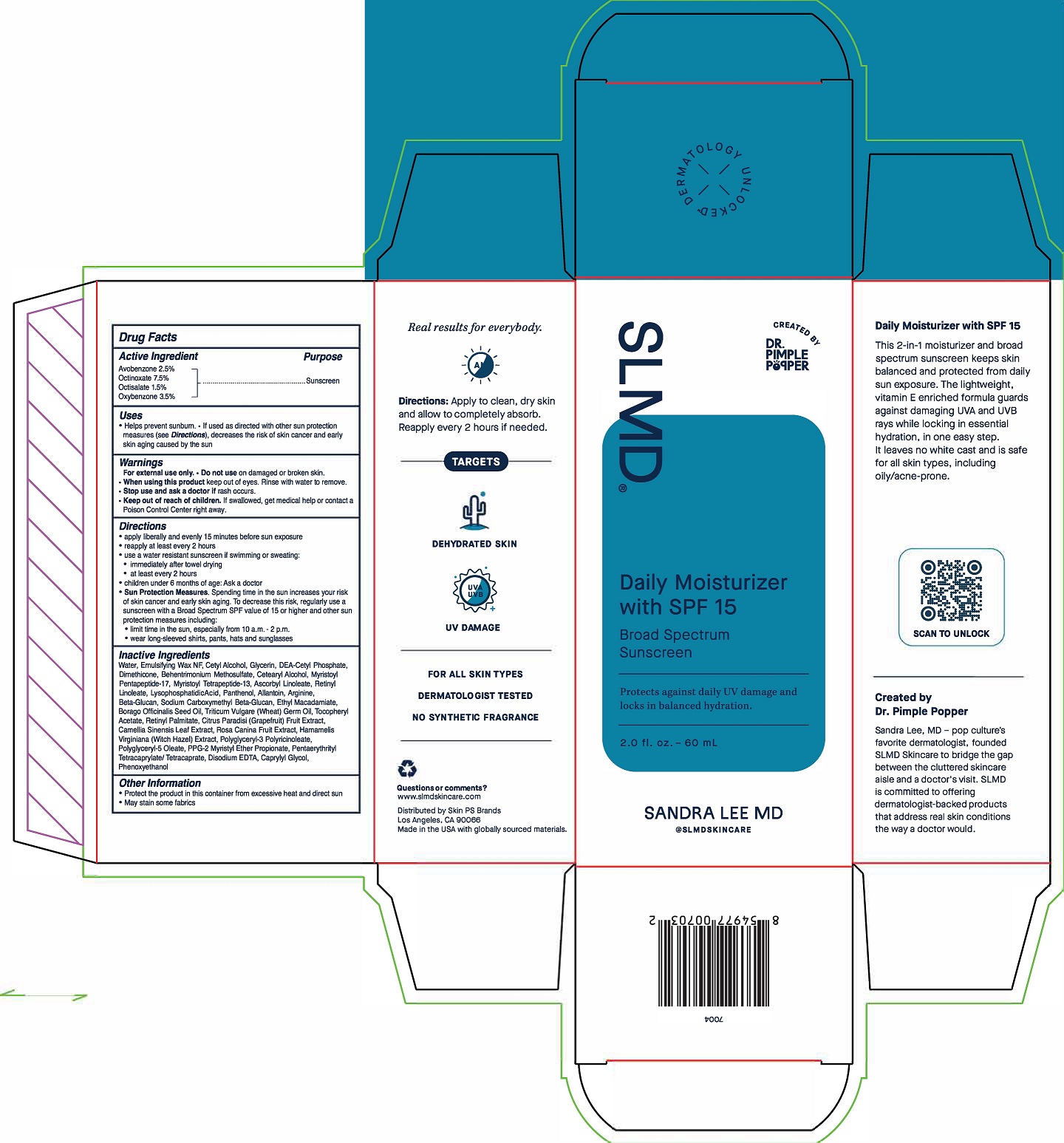 DRUG LABEL: SLMD
NDC: 73318-7008 | Form: CREAM
Manufacturer: Skin PS Brands
Category: otc | Type: HUMAN OTC DRUG LABEL
Date: 20251230

ACTIVE INGREDIENTS: OCTISALATE 1.5 mg/1 g; OXYBENZONE 3.5 mg/1 g; AVOBENZONE 2.5 mg/1 g; OCTINOXATE 7.5 mg/1 g
INACTIVE INGREDIENTS: POLYGLYCERYL-3 RICINOLEATE; CETOSTEARYL ALCOHOL; RETINYL LINOLEATE; ARGININE; BORAGO OFFICINALIS SEED; 1,3-BETA-GLUCAN SYNTHASE COMPONENT FKS1; WHEAT GERM OIL; CAMELLIA SINENSIS FLOWER; GLYCERIN; SODIUM CARBOXYMETHYL .BETA.-GLUCAN (DS 0.65-0.85); DIMETHICONE; ETHYL MACADAMIATE; CITRUS PARADISI FRUIT OIL; ROSA CANINA FRUIT OIL; CAPRYLYL GLYCOL; CETYL ALCOHOL; MYRISTOYL PENTAPEPTIDE-4; PENTAERYTHRITYL TETRACAPRYLATE/TETRACAPRATE; PANTHENOL; VITAMIN A PALMITATE; DIETHANOLAMINE CETYL PHOSPHATE; ALLANTOIN; POLYSORBATE 60; .ALPHA.-TOCOPHEROL ACETATE, D-; WATER; HAMAMELIS VIRGINIANA WHOLE; PPG-2 MYRISTYL ETHER PROPIONATE; PHENOXYETHANOL; ASCORBYL LINOLEATE; LYSOPHOSPHATIDIC ACID; BEHENTRIMONIUM METHOSULFATE; MYRISTOYL PENTAPEPTIDE-17; POLYGLYCERYL-5 TRIOLEATE; EDETATE DISODIUM

Daily Moisturizer with SPF 15

Drug Facts

Active Ingredient

Avobenzone 2.5%

Octinoxate 7.5%

Octisalate 1.5%

Oxybenzone 3.5%

Purpose

Sunscreen

Uses

- Helps prevent sunburn.
- If used as directed with other sun protection measures (see Directions), decreases the risk of skin cancer and early skin aging caused by the sun

Warnings

For external use only.

- Do not useon damaged or broken skin.

WHEN USING

- When using this productkeep out of eyes. Rinse with water to remove.

- Stop use and ask a doctorif rash occurs.

- Keep out of reach of children. If swallowed, get medical help or contact a Poison Control Center right away.

Directions

- apply liberally and evenly 15 minutes before sun exposure.
- reapply at least every 2 hours
- use a water resistant sunscreen if swimming or sweating:
- immediately after towel drying
- at least every 2 hours
- children under 6 months of age: Ask a doctor
- Sun Protection Measures: Spending time in the sun increases your risk of skin cancer and early skin aging. To decrease this risk, regularly use a sunscreen with a Broad Spectrum SPF value of 15 or higher and other sun protection measures including:
- limit time in the sun, especially from 10 a.m. - 2 p.m.
- wear long-sleeved shirts, pants, hats and sunglasses

Inactive Ingredients

Water, Emulsifying Wax NF, Cetyl Alcohol, Glycerin, DEA-Cetyl Phosphate, Dimethicone, Behentrimonium Methosulfate, Cetearyl Alcohol, Myristol Pentapeptide-17, Myristol Pentapeptide-13, Ascorbyl Loneleate, Retinyl Linoleate, Lysophophatidic Acid, Penthonol, Allantoin, Arginine, Beta-Glucan, Sodium Carboxymethyl Beta-Glucan, Ethyl Macadamiate, Borago Officinail Seed OPil, Tiricum Vulgare (Wheat) Germ Oil, Tocopheryl Acetate, Retinyl Palmitate, Citrus Paradisi (Grapefruit) Fruit Extract, Camellia Sinensis Leaf Extract, Rosa Canina Fruit Extract, Hamamelis Virginiana (Witch Hazel) Extract, Polyglyceryl-3 Polyricinoleate, Polyglyceryl-5 Oleate, PPG-2 Myristyl Ether Propionate, Pentaerythrityl Tetracaprylate/Tetracaprate, Disodium EDTA, Caprylyl Glycol, Phenoxyethanol

Other Information

- Protect the product in this container from excessive heat and direct sun
- May stain some fabrics

SLMD®

CREATED BY

DR. PIMPLE POPPER

Daily Moisturizer with SPF 15

Broad Spectrum Sunscreen

Protects against daily UV damage and locks in balanced hydration.

2.0 fl. oz. - 60 mL

SANDRA LEE MD

@SLMDSKINCARE

Unit Carton:

Tube:

Real results for everybody.

Directions: Apply to clean, dry skin and allow to completely absorb. Reapply every 2 hours if needed.

TARGETS

DEHYDRATE SKIN

UV DAMAGE

FOR ALL SKIN TYPES

DERMATOLOGIST TESTED

NO SYNTHETIC FRAGRANCE

Question or comments?

www.slndskincare.com

Distributed by Skin PS Brands

Los Angeles, CA 90066

Made in the USA with globally sourced materials.

Daily Mositurizer with SPF 15

This 2-in-1 moisturizer and broad spectrum sunscreen keeps skin balanced and protected from daily sun exposure. The lighweight, vitamin E enriched formula guards against damaging UVA and UVB rays while locking in essential hydration, in one easy step. It leaves no white case and is safe for all skin types, including oily/acne-prone.

Created by Dr. Pimple Popper

Sandra Lee, MD - pop culture's favorite dermatologist, founded SLMD Skincare to bridge the gap between the cluttered skincare aisle and a doctor's visit. SLMD is committed to offering dermatologist-backed products that address real skin conditions the way a doctor would.